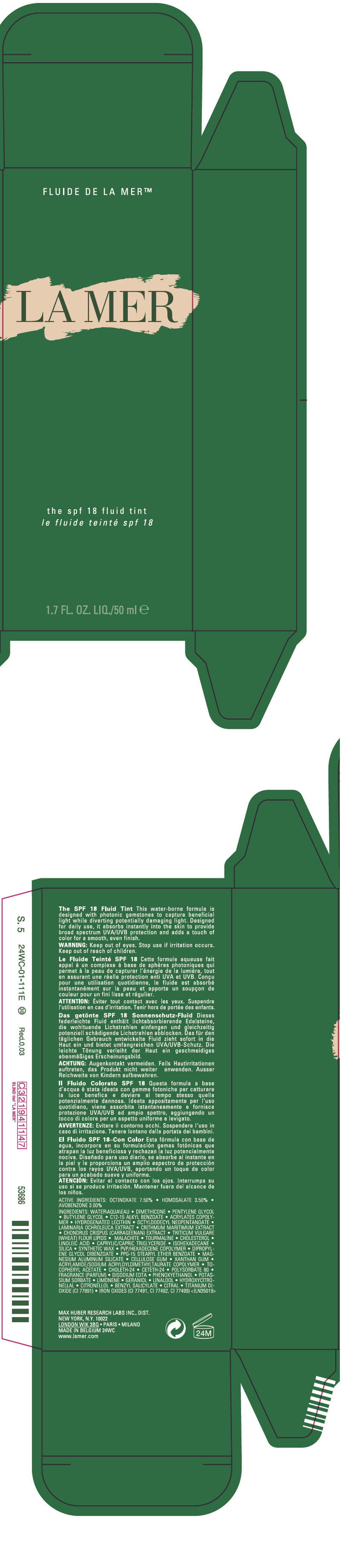 DRUG LABEL: THE SPF 18 FLUID TINT
NDC: 65966-918 | Form: LOTION
Manufacturer: MAX HUBER RESEARCH LAB INC
Category: otc | Type: HUMAN OTC DRUG LABEL
Date: 20120612

ACTIVE INGREDIENTS: OCTINOXATE 7.5 mL/100 mL; HOMOSALATE 3.5 mL/100 mL; AVOBENZONE 3 mL/100 mL
INACTIVE INGREDIENTS: WATER; DIMETHICONE; PENTYLENE GLYCOL; BUTYLENE GLYCOL; ALKYL (C12-15) BENZOATE; OCTYLDODECYL NEOPENTANOATE; LAMINARIA OCHROLEUCA; CRITHMUM MARITIMUM; CHONDRUS CRISPUS; WHEAT; CHOLESTEROL; LINOLEIC ACID; MEDIUM-CHAIN TRIGLYCERIDES; ISOHEXADECANE; SILICON DIOXIDE; DIPROPYLENE GLYCOL DIBENZOATE; PPG-15 STEARYL ETHER BENZOATE; MAGNESIUM ALUMINUM SILICATE; CARBOXYMETHYLCELLULOSE SODIUM; XANTHAN GUM; .ALPHA.-TOCOPHEROL ACETATE; CHOLETH-24; CETETH-24; POLYSORBATE 80; EDETATE DISODIUM; PHENOXYETHANOL; POTASSIUM SORBATE; GERANIOL; LINALOOL, (+/-)-; HYDROXYCITRONELLAL; .BETA.-CITRONELLOL, (R)-; BENZYL SALICYLATE; CITRAL; TITANIUM DIOXIDE; FERRIC OXIDE RED; FERRIC OXIDE YELLOW; FERROSOFERRIC OXIDE

THE SPF 18 FLUID TINT
SUNSCREEN MAKEUP

WARNING

Keep out of eyes.

Stop use if irritation occurs.

Keep out of reach of children.

ACTIVE INGREDIENTS

OCTINOXATE 7.50% ∙ HOMOSALATE 3.50% ∙ AVOBENZONE 3.00%

INGREDIENTS

WATER\AQUA\EAU ∙ DIMETHICONE ∙ PENTYLENE GLYCOL ∙ BUTYLENE GLYCOL ∙ C12-15 ALKYL BENZOATE ∙ ACRYLATES COPOLYMER ∙ HYDROGENATED LECITHIN ∙ OCTYLDODECYL NEOPENTANOATE ∙ LAMINARIA OCHROLEUCA EXTRACT ∙ CRITHMUM MARITIMUM EXTRACT ∙ CHONDRUS CRISPUS (CARRAGEENAN) EXTRACT ∙ TRITICUM VULGARE (WHEAT) FLOUR LIPIDS ∙ MALACHITE ∙ TOURMALINE ∙ CHOLESTEROL ∙ LINOLEIC ACID ∙ CAPRYLIC/CAPRIC TRIGLYCERIDE ∙ ISOHEXADECANE ∙ SILICA ∙ SYNTHETIC WAX ∙ PVP/HEXADECENE COPOLYMER ∙ DIPROPYLENE GLYCOL DIBENZOATE ∙ PPG-15 STEARYL ETHER BENZOATE ∙ MAGNESIUM ALUMINUM SILICATE ∙ CELLULOSE GUM ∙ XANTHAN GUM ∙ ACRYLAMIDE/SODIUM ACRYLOYLDIMETHYLTAURATE COPOLYMER ∙ TOCOPHERYL ACETATE ∙ CHOLETH-24 ∙ CETETH-24 ∙ POLYSORBATE 80 ∙ FRAGRANCE (PARFUM) ∙ DISODIUM EDTA ∙ PHENOXYETHANOL ∙ POTASSIUM SORBATE ∙ LIMONENE ∙ GERANIOL ∙ LINALOOL ∙ HYDROXYCITRONELLAL ∙ CITRONELLOL ∙ BENZYL SALICYLATE ∙ CITRAL ∙ TITANIUM DIOXIDE (CI 77891) ∙ IRON OXIDES (CI 77491, CI 77492, CI 77499) <ILN35019>

PRINCIPAL DISPLAY PANEL - 50 ml Bottle Carton

LA MER

the spf 18 fluid tint

1.7 FL. OZ. LIQ./50 ml e